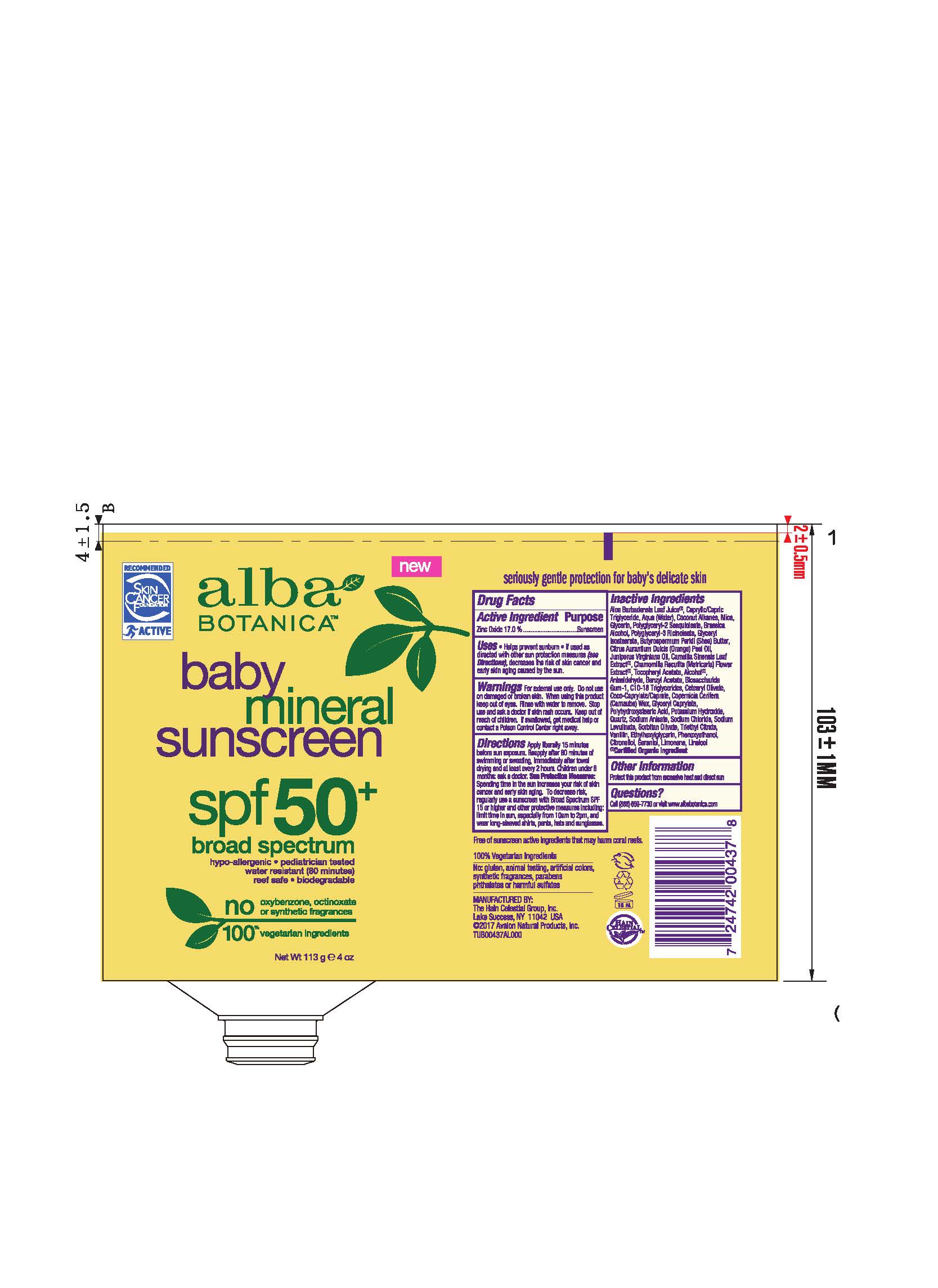 DRUG LABEL: AL0043700 Alba Botanica Baby Mineral Sunscreen SPF50
NDC: 61995-2437 | Form: LOTION
Manufacturer: The Hain Celestial Group, Inc.
Category: otc | Type: HUMAN OTC DRUG LABEL
Date: 20210205

ACTIVE INGREDIENTS: ZINC OXIDE 17 g/100 g
INACTIVE INGREDIENTS: MICA; BIOSACCHARIDE GUM-1; ORANGE OIL; POLYGLYCERYL-2 SESQUIISOSTEARATE; CARNAUBA WAX; ALCOHOL; PHENOXYETHANOL; ALOE VERA LEAF; COCONUT ALKANES; GLYCERIN; POLYGLYCERYL-3 RICINOLEATE; WATER; SHEA BUTTER; GREEN TEA LEAF; COCO-CAPRYLATE/CAPRATE; SODIUM CHLORIDE; SORBITAN SESQUIOLEATE; POLYHYDROXYSTEARIC ACID (2300 MW); MEDIUM-CHAIN TRIGLYCERIDES; .ALPHA.-TOCOPHEROL ACETATE; GLYCERYL ISOSTEARATE; CETEARYL OLIVATE; GLYCERYL CAPRYLATE; C10-18 TRIGLYCERIDES; ETHYLHEXYLGLYCERIN; CHAMOMILE; JUNIPERUS VIRGINIANA OIL

Alba Botanica Baby Mineral Sunscreen SPF 50

Active Ingredient

Zinc Oxide - 17.0%

DOSAGE AND ADMINISTRATION

Apply liberally 15 minutes before sun exposure. Reapply after 80 minutes of swimming or sweating, immediately after towel drying and at least every 2 hours. Children under 6 months: ask a doctor.

PURPOSE

Sunscreen

WARNINGS

For external use only. Do not use on damaged or broken skin. When using this product keep out of eyes. Rinse with water to remove. Stop use and ask a doctor if skin rash occurs.

Keep out of reach of children. If swallowed get medical help or contact Poison Center right away.

INACTIVE INGREDIENT

Water, Caprylic Capric Triglyceride, Coconut Alkanes, Mica, Glycerin, Polyglyceryl-2 Sesquioleate, Polyglyceryl-3 Ricinoleate, Glyceryl Isostearate, Aloe Barbadensis Leaf Juice(1), Butyrospermum Parkii (Shea) Butter,Citrus Aurantium Dulcis (Orange) Peel Oil, Copernica Cerifera (Carnauba) Wax, Juniperus Virginiana Oil, Camilla Sinensis Leaf Extract (1), Chamomilla Recutita (Matricaria) Flower Extract (1), Brassica Alcohol, Coco-Caprylate/Caprate, Sodium Chloride, Alcohol (1), Polyhydroxystearic Acid,Tocopheryl Acetate, Biosaccharide Gum-1,C10-18 Triglycerides, Cetearyl Olivate, Glyceryl Caprylate, Potassium Hydroxide, Quartz, Sodium Anisate, Sorbitan Olivate, Ethylhexylglycerin.

(1) Certified Organicf Ingredient

INDICATIONS AND USAGE

Helps prevents sunburns. If used as directed with other sun protection measures, decreases risk of skin cancer and early skin aging caused by sun exposure. Skin Protection Measures: Spending time in the sun increases your risk of skin cancer and early skin aging. To decrease risk, regularly use sunscreen with Broad Spectrum SPF 15 or higher and other protective measures including: limit time in sun, especially from10am to 2pm, and wear long sleeved shirts, pants, hats and sunglases.